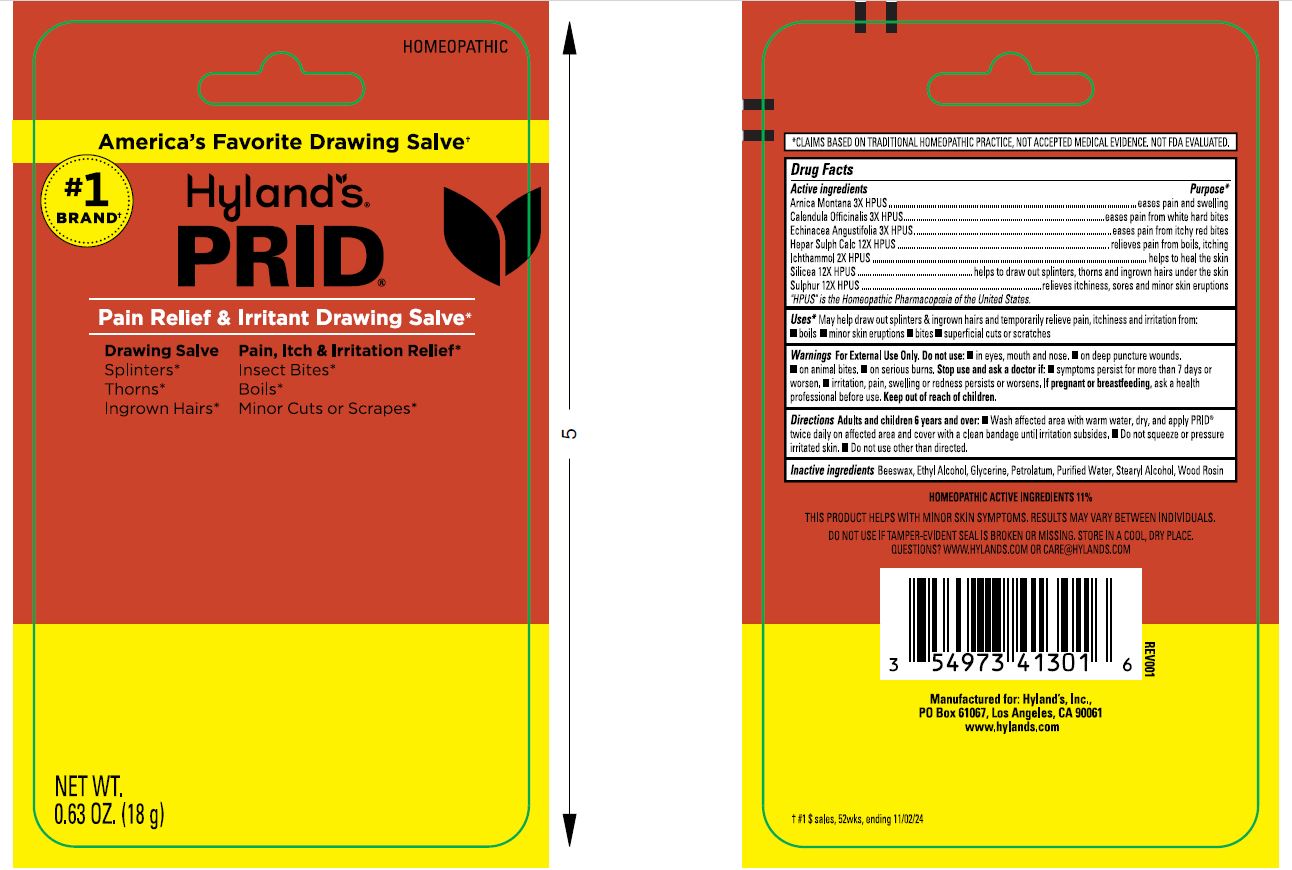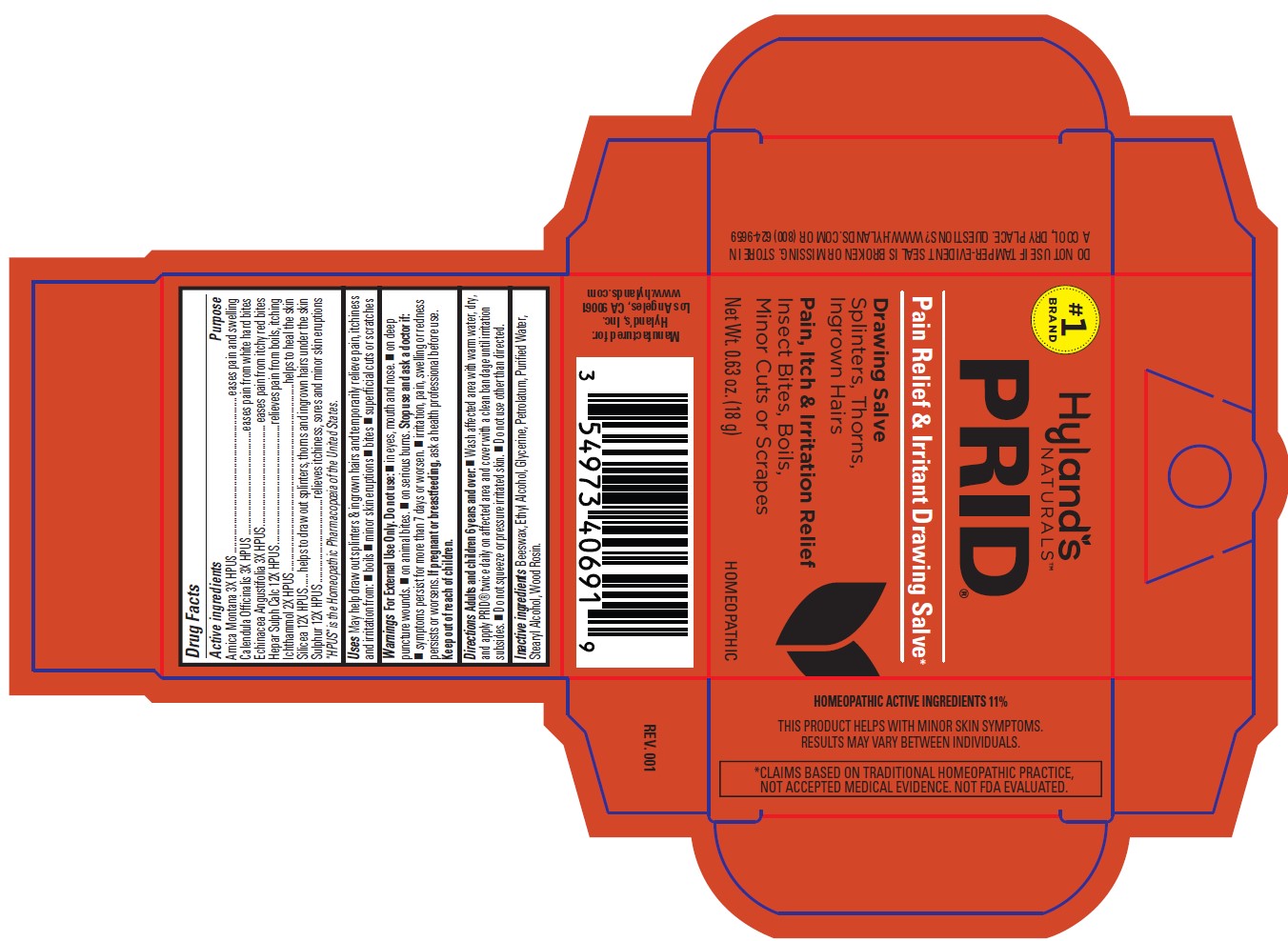 DRUG LABEL: Prid
NDC: 54973-4099 | Form: SALVE
Manufacturer: Hyland's Inc.
Category: homeopathic | Type: HUMAN OTC DRUG LABEL
Date: 20260127

ACTIVE INGREDIENTS: CALCIUM SULFIDE 12 [hp_X]/1 g; SILICON DIOXIDE 12 [hp_X]/1 g; ECHINACEA ANGUSTIFOLIA 3 [hp_X]/1 g; ARNICA MONTANA 3 [hp_X]/1 g; CALENDULA OFFICINALIS FLOWERING TOP 3 [hp_X]/1 g; ICHTHAMMOL 2 [hp_X]/1 g; SULFUR 12 [hp_X]/1 g
INACTIVE INGREDIENTS: PETROLATUM; ALCOHOL; YELLOW WAX; WATER; STEARYL ALCOHOL; ROSIN; GLYCERIN

Hyland's Prid Topical Ointment

PURPOSE

May help draw out splinters & ingrown hairs and temporarily relieve pain, itchiness and irritation from: boils, minor skin eruptions, bites superficial cuts or scratches

Drug Facts

Active ingredients | Purpose
Arnica Montana 3X HPUS | eases pain and swelling
Calendula Officinalis 3X HPUS | eases pain from white hard bites
Echinacea Angustifolia 3X HPUS | eases pain from itchy red bites
Hepar Sulph Calc 12X HPUS | relieves pain from boils, itching
Ichthammol 2X HPUS | helps to heal the skin
Silicea 12X HPUS | helps to draw out splinters, thorns and ingrown hairs under the skin
Sulphur 12X HPUS | relieves itchiness, sores and minor skin eruptions

"HPUS" is the Homeopathic Pharmacopoeia of the United States.

Uses

May help draw out splinters & ingrown hairs and temporarily relieve pain, itchiness and irritation from: ■ boils ■ minor skin eruptions ■ bites ■ superficial cuts or scratches

Warnings

For External Use Only.

Do not use

■ in eyes, mouth and nose. ■ on deep puncture wounds. ■ on animal bites. ■ on serious burns.

Stop use and ask a doctor if

■ symptoms persist for more than 7 days or worsen. ■ irritation, pain, swelling or redness persists or worsens.

If pregnant or breastfeeding

ask a health professional before use.

Directions

Adults and children 6 years and over

■ Wash affected area with warm water, dry, and apply PRID® twice daily on affected area and cover with a clean bandage until irritation subsides. ■ Do not squeeze or pressure irritated skin. ■ Do not use other than directed

Inactive ingredients

Beeswax, Ethyl Alcohol, Glycerine, Petrolatum, Purified Water, Stearyl Alcohol, Wood Rosin.

Package Label

#1

Brand

Hyland's

NATURALS

PRID

Pain Relief & Irritant Drawing Salve*

Drawing Salve
Splinters, Thorns, Ingrown Hairs

Pain, Itch & Irritation Relief
Insect Bites, Boils,
Minor Cuts or Scrapes

Net Wt. 0.63 oz. (18 g)

HOMEOPATHIC